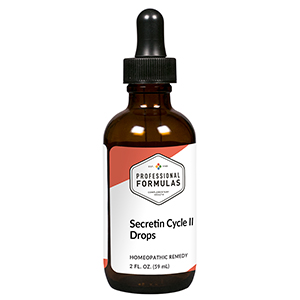 DRUG LABEL: Secretin Cycle II Drops
NDC: 63083-2164 | Form: LIQUID
Manufacturer: Professional Complementary Health Formulas
Category: homeopathic | Type: HUMAN OTC DRUG LABEL
Date: 20190815

ACTIVE INGREDIENTS: SUS SCROFA ADRENAL GLAND 30 [hp_X]/59 mL; BOS TAURUS BRAIN 30 [hp_X]/59 mL; BOS TAURUS HYPOTHALAMUS 30 [hp_X]/59 mL; BOS TAURUS LARGE INTESTINE 30 [hp_X]/59 mL; BEEF KIDNEY 30 [hp_X]/59 mL; BEEF LIVER 30 [hp_X]/59 mL; BOS TAURUS LYMPH VESSEL 30 [hp_X]/59 mL; BOS TAURUS SPLEEN 30 [hp_X]/59 mL; HYSSOPUS OFFICINALIS WHOLE 30 [hp_X]/59 mL; SECRETIN, UNSPECIFIED 60 [hp_X]/59 mL
INACTIVE INGREDIENTS: ALCOHOL; WATER

C164

ACTIVE INGREDIENTS

Adrenal 30X
Brain 30X
Hypothalamus 30X
Intestine 30X
Kidney 30X
Liver 30X
Lymph 30X
Spleen 30X
Thymus 30X
Secretin 60X, 100X, 200X, 500X

QUESTIONS

Professional Formulas

PO Box 2034 Lake Oswego, OR 97035

INDICATIONS

For the temporary relief of indigestion or heartburn.*

PURPOSE

*Claims based on traditional homeopathic practice, not accepted medical evidence. Not FDA evaluated.

WARNINGS

In case of overdose, get medical help or contact a poison control center right away.

Keep out of the reach of children.

PREGNANCY OR BREAST FEEDING

If pregnant or breastfeeding, ask a healthcare professional before use.

DIRECTIONS

Place drops under tongue 30 minutes before/after meals. Adults and children 12 years and over: Take 10 drops up to 3 times per day. Consult a physician for use in children under 12 years of age.

OTHER INFORMATION

Tamper resistant. If seal is broken, do not use. After opening, close container tightly and store at room temperature away from heat.

INACTIVE INGREDIENTS

20% ethanol, purified water.

LABEL

Est 1985

Professional Formulas

Complementary Health

Secretin Cycle II Drops

Homeopathic Remedy

2 FL. OZ. (59 mL)